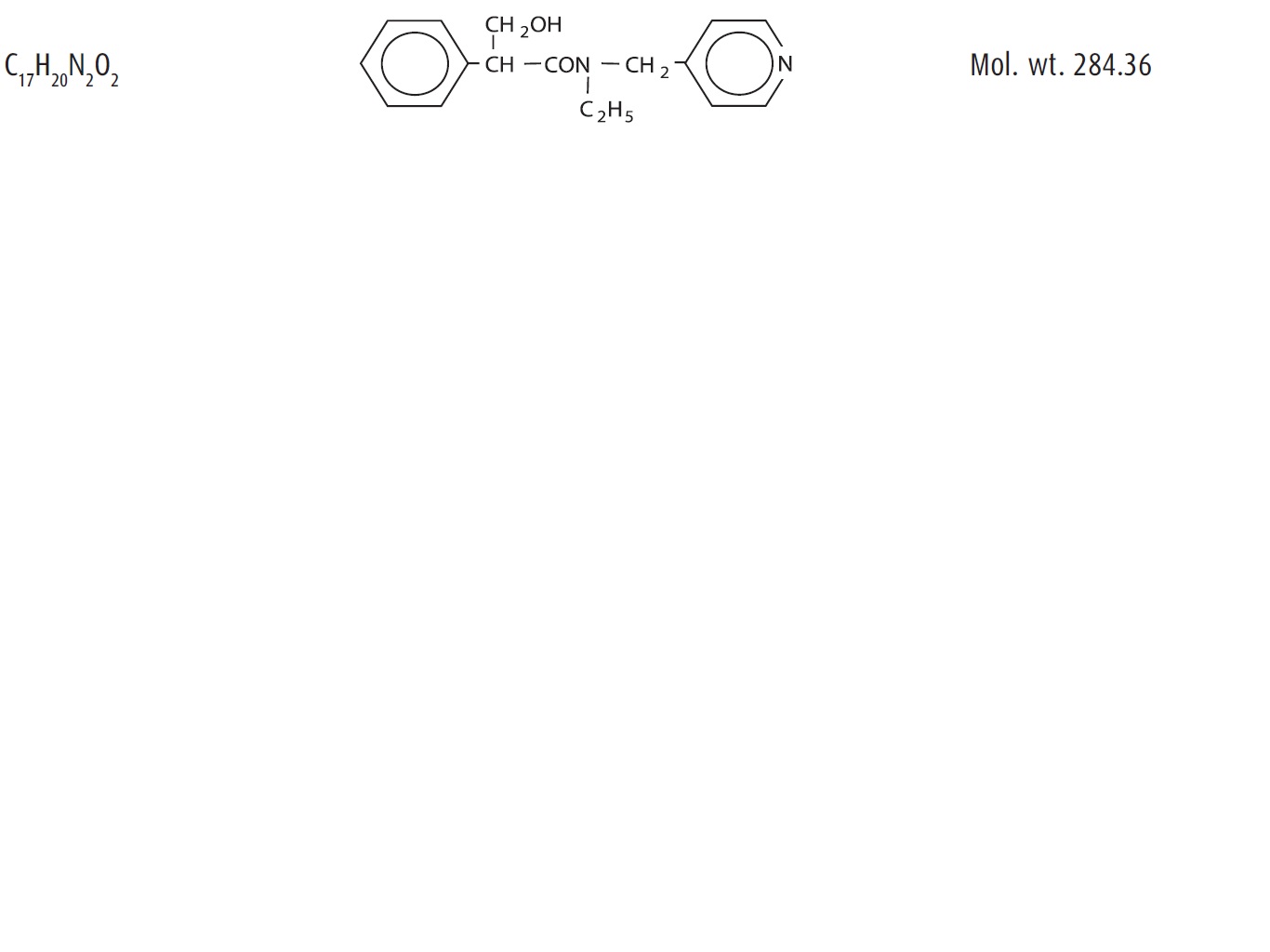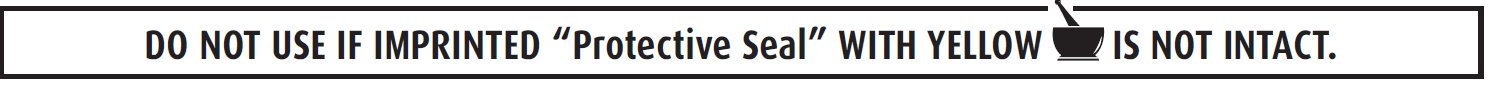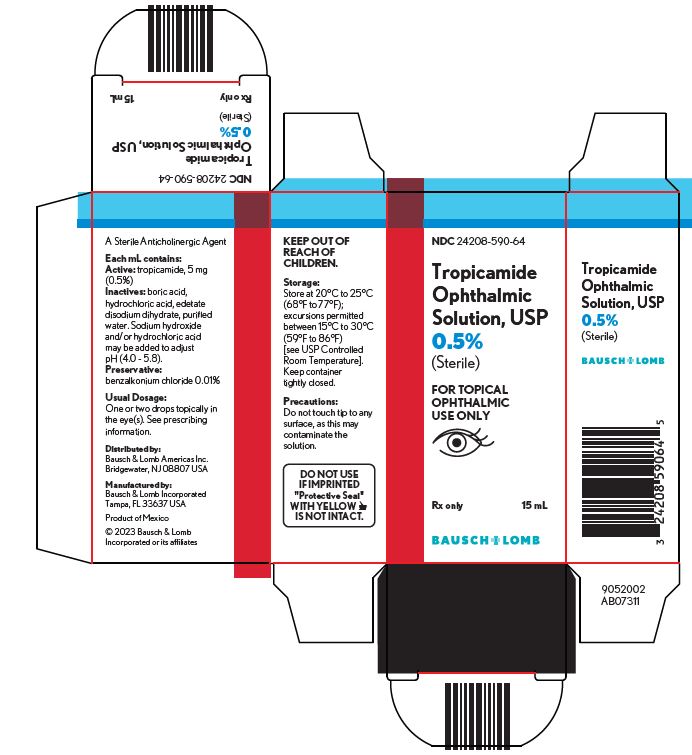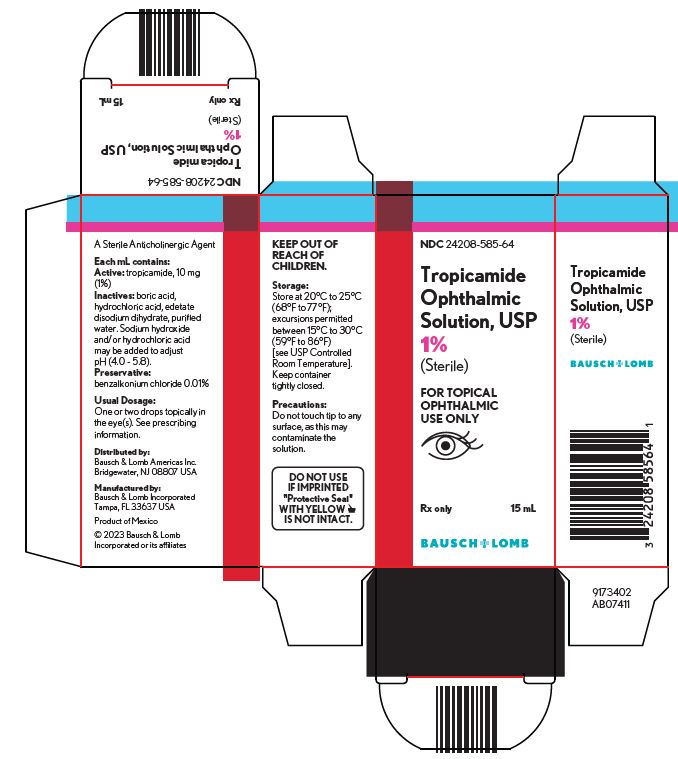 DRUG LABEL: Tropicamide
NDC: 24208-590 | Form: SOLUTION/ DROPS
Manufacturer: Bausch & Lomb Incorporated
Category: prescription | Type: HUMAN PRESCRIPTION DRUG LABEL
Date: 20230901

ACTIVE INGREDIENTS: TROPICAMIDE 5 mg/1 mL
INACTIVE INGREDIENTS: BENZALKONIUM CHLORIDE; BORIC ACID; EDETATE DISODIUM; HYDROCHLORIC ACID; WATER; SODIUM HYDROXIDE

Tropicamide Ophthalmic
Solution, USP
(Sterile)

Rx only

DESCRIPTION

Tropicamide ophthalmic solution, USP is an anticholinergic prepared as a sterile topical ophthalmic solution in two strengths. The active ingredient is represented by the following chemical structure:

Chemical name:
Benzeneacetamide, N-ethyl-α-(hydroxymethyl)-N-(4-pyridinylmethyl)-

Each mL contains:

Active: tropicamide 5 mg (0.5%) or 10 mg (1%); Inactives: boric acid, hydrochloric acid, edetate disodium dihydrate, purified water. Sodium hydroxide and/or hydrochloric acid (to adjust pH) pH range 4.0 - 5.8. Preservative: benzalkonium chloride 0.01%.

CLINICAL PHARMACOLOGY

This anticholinergic preparation blocks the responses of the sphincter muscle of the iris and the ciliary muscle to cholinergic stimulation, dilating the pupil [mydriasis]. The stronger preparation (1%) also paralyzes accommodation. This preparation acts in 15-30 minutes, and the duration of activity is approximately 3-8 hours. Complete recovery from mydriasis in some individuals may require 24 hours. The weaker strength (0.5%) may be useful in producing mydriasis with only slight cycloplegia. Heavily pigmented irides may require more doses than lightly pigmented irides.

INDICATIONS AND USAGE

For mydriasis and cycloplegia for diagnostic procedures.

CONTRAINDICATIONS

Contraindicated in persons showing hypersensitivity to any component of this preparation.

WARNINGS

FOR TOPICAL OPHTHALMIC USE ONLY. NOT FOR INJECTION.

This preparation may cause CNS disturbances which may be dangerous in pediatric patients. The possibility of psychotic reaction and behavioral disturbance due to hypersensitivity to anticholinergic drugs should be considered.

Mydriatics may produce a transient elevation of intraocular pressure.

Remove contact lenses before using.

PRECAUTIONS

General

The lacrimal sac should be compressed by digital pressure for two to three minutes after instillation to reduce excessive systemic absorption.

Information for Patients

Do not touch dropper tip to any surface, as this may contaminate the solution. Patients should be advised not to drive or engage in potentially hazardous activities while pupils are dilated. Patients may experience sensitivity to light and should protect eyes in bright illumination during dilation. Parents should be warned not to get this preparation in their child’s mouth and wash their own hands and the child’s hands following administration.

Drug Interactions

Tropicamide may interfere with the antihypertensive action of carbachol, pilocarpine, or ophthalmic cholinesterase inhibitors.

Carcinogenesis, Mutagenesis, Impairment of Fertility

There have been no long-term studies done using tropicamide in animals to evaluate carcinogenic potential.

Pregnancy

Animal reproduction studies have not been conducted with tropicamide. It is also not known whether tropicamide can cause fetal harm when administered to a pregnant woman or can affect reproduction capacity. Tropicamide should be given to a pregnant woman only if clearly needed.

Nursing Mothers

It is not known whether this drug is excreted in human milk. Because many drugs are excreted in human milk, caution should be exercised when tropicamide is administered to a nursing woman.

Pediatric Use

Tropicamide may rarely cause CNS disturbances which may be dangerous in pediatric patients. Psychotic reactions, behavioral disturbances, and vasomotor or cardiorespiratory collapse in children have been reported with the use of anticholinergic drugs (see WARNINGS). Keep this and all medications out of the reach of children.

Geriatric Use

No overall differences in safety or effectiveness have been observed between elderly and younger patients.

ADVERSE REACTIONS

Ocular
Transient stinging, blurred vision, photophobia and superficial punctate keratitis have been reported with the use of tropicamide. Increased intraocular pressure has been reported following the use of mydriatics.

Non-Ocular
Dryness of the mouth, tachycardia, headache, allergic reactions, nausea, vomiting, pallor, central nervous system disturbances and muscle rigidity have been reported with the use of tropicamide. Psychotic reactions, behavioral disturbances, and vasomotor or cardiorespiratory collapse in children have been reported with the use of anticholinergic drugs.

To report SUSPECTED ADVERSE REACTIONS, contact Bausch & Lomb Incorporated at 1-800-553-5340 or FDA at 1-800-FDA-1088 or www.fda.gov/medwatch.

DOSAGE AND ADMINISTRATION

For refraction, one or two drops of the 1% solution in the eye(s), repeated in five minutes. If patient is not seen within 20 to 30 minutes, an additional drop may be instilled to prolong mydriatic effect. For examination of fundus, one or two drops of the 0.5% solution 15 or 20 minutes prior to examination. Individuals with heavily pigmented irides may require higher strength or more doses. Mydriasis will reverse spontaneously with time, typically in 4 to 8 hours. However, in some cases, complete recovery may take up to 24 hours.

HOW SUPPLIED

Tropicamide ophthalmic solution USP, 1% is supplied in a plastic bottle with a red cap and a controlled drop tip in the following sizes:
  NDC 24208-585-59: 2 mL in a 7.5 mL bottle
  NDC 24208-585-64: 15 mL in a 15 mL bottle
Tropicamide ophthalmic solution USP, 0.5% is supplied in a plastic bottle with a red cap and a controlled drop tip in the following size:
  NDC 24208-590-64: 15 mL in a 15 mL bottle

Storage: Store at 20°C to 25°C (68°F to 77°F); excursions permitted between 15°C to 30°C (59°F to 86°F) [see USP Controlled Room Temperature].
Keep container tightly closed.

Keep out of reach of children.

Distributed by:
Bausch & Lomb Americas Inc.
Bridgewater, NJ 08807 USA

Manufactured by:
Bausch & Lomb Incorporated
Tampa, FL 33637 USA

© 2023 Bausch & Lomb Incorporated or its affiliates

Revised: September 2023

9115807 (Folded)
9115907 (Flat)

PACKAGE/LABEL PRINCIPAL DISPLAY PANEL (Mexico) - 0.5

NDC 24208-590-64

Tropicamide
Ophthalmic
Solution, USP
0.5%
(Sterile)

FOR TOPICAL
OPHTHALMIC
USE ONLY

Rx only

15 mL

BAUSCH + LOMB

9052002

AB07311

PACKAGE/LABEL PRINCIPAL DISPLAY PANEL Mexico 1

NDC 24208-585-64

Tropicamide
Ophthalmic
Solution, USP
1%
(Sterile)

FOR TOPICAL
OPHTHALMIC
USE ONLY

Rx only

15 mL

BAUSCH + LOMB

9173402

AB07411